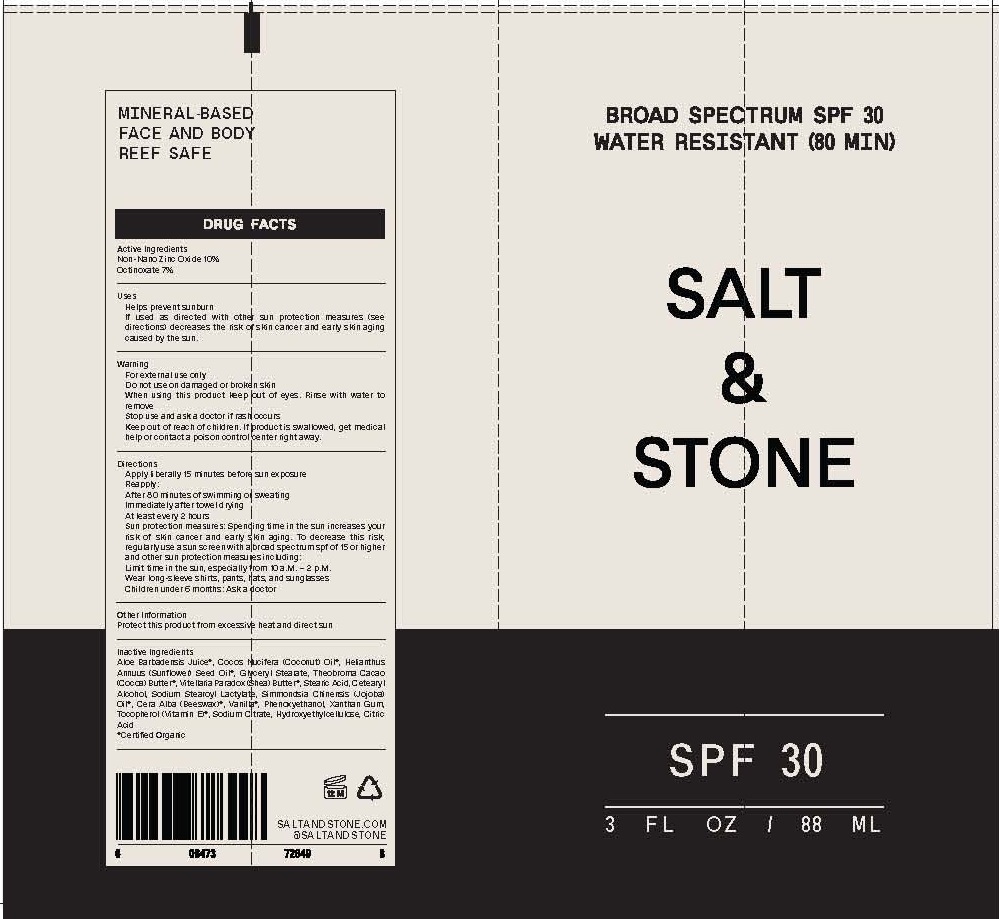 DRUG LABEL: PREMIUM SUNSCREEN
NDC: 71585-105 | Form: LOTION
Manufacturer: SALT AND STONE
Category: otc | Type: HUMAN OTC DRUG LABEL
Date: 20190728

ACTIVE INGREDIENTS: ZINC OXIDE 20 g/100 mL
INACTIVE INGREDIENTS: ALOE VERA LEAF; YELLOW WAX; CETOSTEARYL ALCOHOL; ANHYDROUS CITRIC ACID; COCONUT OIL; GLYCERYL MONOSTEARATE; SUNFLOWER OIL; HYDROXYETHYL CELLULOSE (100 MPA.S AT 2%); PHENOXYETHANOL; JOJOBA OIL; SODIUM CITRATE; SODIUM STEAROYL LACTYLATE; STEARIC ACID; COCOA BUTTER; TOCOPHEROL; VANILLA; SHEA BUTTER; XANTHAN GUM

SALT & STONE PREMIUM SUNSCREEN SPF-30

ACTIVE INGREDIENTS

ZINC OXIDE 20%

PURPOSE

SUNSCREEN

USE

HELPS PREVENT SUNBURN.

WARNINGS

FOR EXTERNAL USE ONLY.

DO NOT USE ON DAMAGED OR BROKEN SKIN.

IF RASH OCCURS, DISCONTINUE USE AND CONSULT A HEALTH CARE PRACTITIONER.

WHEN USING THIS PRODUCT: KEEP OUT OF EYES. RINSE WITH WATER TO REMOVE.

KEEP OUT OF REACH OF CHILDREN. IF PRODUCT IS SWALLOWED, GET MEDICAL HELP OR CONTACT A POISON CONTROL CENTER RIGHT AWAY.

DIRECTIONS

For use on children less than 6 months of age, consult a health care practitioner. Apply liberally/generously (and evenly) 15 minutes before sun exposure. Reapply at least every 2 hours. Reapply after 80 minutes of swimming or sweating. Reapply immediately after towel drying. Sun Protection Measures. Spending time in the sun increases your risk of skin cancer and early skin aging. To decrease this risk, regularly use a sunscreen with a Broad Spectrum SPF of 15 or higher and other sun protection measures, including Limit time in the sun, especially from 10am - 2pm. wear long-sleeved shirts, pants, hats and sunglasses.

INACTIVE INGREDIENTS

*Aloe Barbadensis Juice, *Cera Alba (Beeswax), Cetearyl Alcohol, Citric Acid, *Cocos Nucifera (Coconut) Oil, Glyceryl Stearate, *Helianthus Annuus (Sunflower) Seed Oil, Hydroxyethylcellulose, Phenoxyethanol, *Simmondsia Chinesnsis (Jojoba) Oil, Sodium Citrate, Sodium Stearoyl Lactylate, Stearic Acid, *Theobroma Cacao (Cocoa) Butter, *Tocopherol (Vitamin E), *Vanilla, *Vitellaria Paradox (Shea) Butter, Xanthan Gum

*Certified Organic

OTHER INFORMATION

- PROTECT THIS PRODUCT FROM EXCESSIVE HEAT AND DIRECT SUN

QUESTIONS OR COMMENTS?

CALL TOLL FREE 888 952 4250